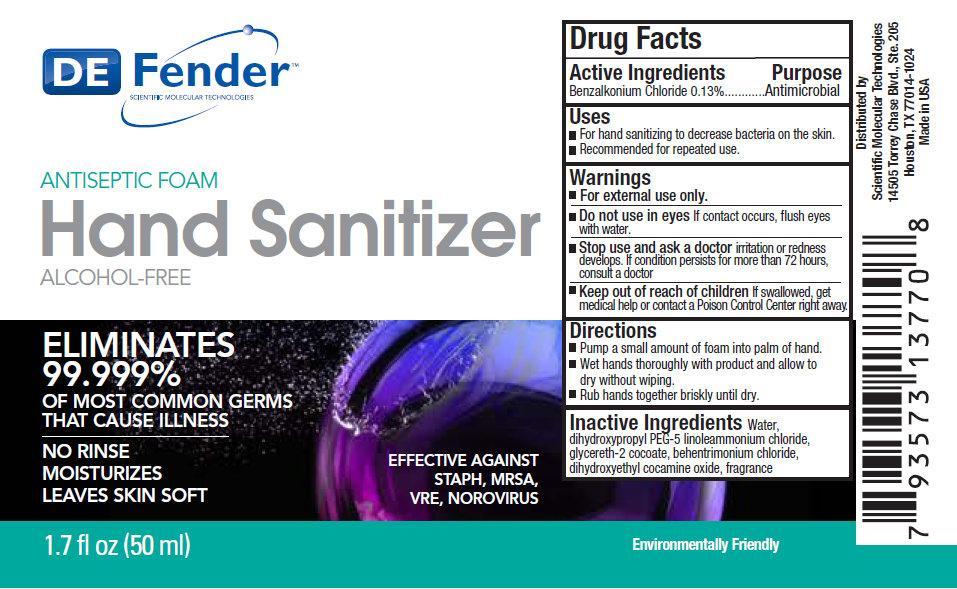 DRUG LABEL: DEFENDER Antiseptic Foam Hand Sanitizer Alcohol-Free
NDC: 42953-002 | Form: LIQUID
Manufacturer: Scientific Molecular Technologies
Category: otc | Type: HUMAN OTC DRUG LABEL
Date: 20210601

ACTIVE INGREDIENTS: BENZALKONIUM CHLORIDE 1.3 mg/1 mL
INACTIVE INGREDIENTS: WATER; DIHYDROXYPROPYL PEG-5 LINOLEAMMONIUM CHLORIDE; GLYCERETH-2 COCOATE; BEHENTRIMONIUM CHLORIDE; DIHYDROXYETHYL COCAMINE OXIDE

DEFENDER Antiseptic Foam Hand Sanitizer Alcohol-Free

Active Ingredients

Benzalkonium Chloride 0.13%

Purpose

Antimicrobial

Uses

- For hand sanitizing to decrease bacteria on the skin.
- Recommended for repeated use.

Warnings

- For external use only.

Do not use in eyes

if contact occurs, flush eyes with water.

Stop use and ask a doctor

if irritation or redness develops. If condition persists for more than 72 hours, consult a doctor.

Keep out of reach of children

If swallowed, get medical help or contact a Poison Control Center right away.

Directions

- Pump a small amount of foam into palm of hand.
- Wet hands thoroughly with product and allow to dry without wiping.
- Rub hands together briskly until dry.

Inactive Ingredients

Water, dihydroxypropyl PEG-5 linoleammonium chloride, glycereth-2 cocoate, behentrimonium chloride, dihydroxyethyl cocamine oxide, fragrance

PACKAGE LABEL

DE Fender SCIENTIFIC MOLECULAR TECHNOLOGIES ANTISEPTIC FOAM Hand Sanitizer ALCOHOL-FREE ELIMINATES 99.999% OF MOST COMMON GERMS THAT CAUSES ILLNESS NO RINSE MOISTURIZES LEAVES SKIN SOFT EFFECTIVE AGAINST STAPH, MRSA, VRE, NOROVIRUS 1.7 fl oz (50 ml)